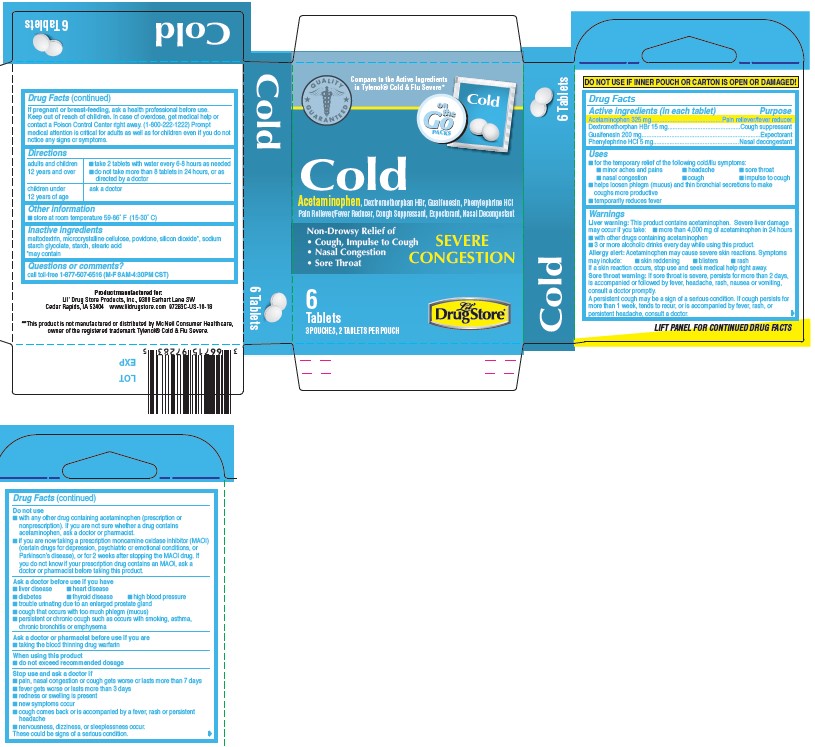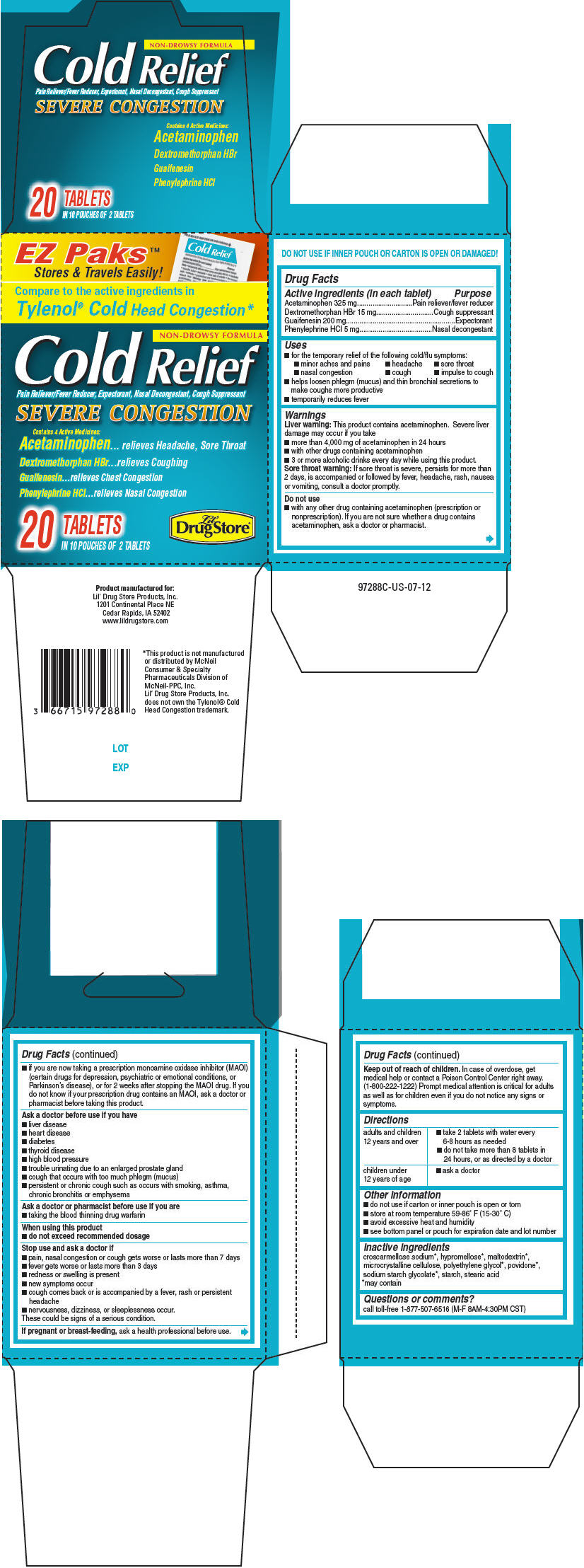 DRUG LABEL: Lil Drug Store Cold Relief
NDC: 66715-9728 | Form: TABLET
Manufacturer: Lil' Drug Store Products, Inc.
Category: otc | Type: HUMAN OTC DRUG LABEL
Date: 20210721

ACTIVE INGREDIENTS: ACETAMINOPHEN 325 mg/1 1; DEXTROMETHORPHAN HYDROBROMIDE 15 mg/1 1; GUAIFENESIN 200 mg/1 1; PHENYLEPHRINE HYDROCHLORIDE 5 mg/1 1
INACTIVE INGREDIENTS: MALTODEXTRIN; MICROCRYSTALLINE CELLULOSE; POVIDONE, UNSPECIFIED; SODIUM STARCH GLYCOLATE TYPE A CORN; STARCH, CORN; STEARIC ACID

Lil' Drug Store® Cold Relief

Drug Facts

ACTIVE INGREDIENT

Active ingredients (in each tablet) | Purpose
Acetaminophen 325 mg | Pain reliever/fever reducer
Dextromethorphan HBr 15 mg | Cough suppressant
Guaifenesin 200 mg | Expectorant
Phenylephrine HCl 5 mg | Nasal decongestant

Uses

- for the temporary relief of the following cold/flu symptoms:
  - minor aches and pains
  - headache
  - sore throat
  - nasal congestion
  - cough
  - impulse to cough
- helps loosen phlegm (mucus) and thin bronchial secretions to make coughs more productive
- temporarily reduces fever

Warnings

Liver warning

This product contains acetaminophen. Severe liver damage may occur if you take

- more than 4,000 mg of acetaminophen in 24 hours
- with other drugs containing acetaminophen
- 3 or more alcoholic drinks every day while using this product.

Sore throat warning

If sore throat is severe, persists for more than 2 days, is accompanied or followed by fever, headache, rash, nausea or vomiting, consult a doctor promptly.

Do not use

- with any other drug containing acetaminophen (prescription or nonprescription). If you are not sure whether a drug contains acetaminophen, ask a doctor or pharmacist.
- if you are now taking a prescription monoamine oxidase inhibitor (MAOI) (certain drugs for depression, psychiatric or emotional conditions, or Parkinson's disease), or for 2 weeks after stopping the MAOI drug. If you do not know if your prescription drug contains an MAOI, ask a doctor or pharmacist before taking this product.

Ask a doctor before use if you have

- liver disease
- heart disease
- diabetes
- thyroid disease
- high blood pressure
- trouble urinating due to an enlarged prostate gland
- cough that occurs with too much phlegm (mucus)
- persistent or chronic cough such as occurs with smoking, asthma, chronic bronchitis or emphysema

Ask a doctor or pharmacist before use if you are

- taking the blood thinning drug warfarin

When using this product

- do not exceed recommended dosage

Stop use and ask a doctor if

- pain, nasal congestion or cough gets worse or lasts more than 7 days
- fever gets worse or lasts more than 3 days
- redness or swelling is present
- new symptoms occur
- cough comes back or is accompanied by a fever, rash or persistent headache
- nervousness, dizziness, or sleeplessness occur.

These could be signs of a serious condition.

PREGNANCY OR BREAST FEEDING

If pregnant or breast-feeding, ask a health professional before use.

Keep out of reach of children. In case of overdose, get medical help or contact a Poison Control Center right away. (1-800-222-1222) Prompt medical attention is critical for adults as well as for children even if you do not notice any signs or symptoms.

Directions

adults and children 12 years and over | - take 2 tablets with water every 6-8 hours as needed - do not take more than 8 tablets in 24 hours, or as directed by a doctor
children under 12 years of age | - ask a doctor

Other information

- do not use if carton or inner pouch is open or torn
- store at room temperature 59-86° F (15-30° C)
- avoid excessive heat and humidity
- see bottom panel or pouch for expiration date and lot number

Inactive ingredients

maltodextrin, microcrystalline cellulose, povidone, sodium starch glycolate, starch, stearic acid

Questions or comments?

call toll-free 1-877-507-6516 (M-F 8AM-4:30PM CST)

PRINCIPAL DISPLAY PANEL - 6 Tablet Pouch Carton

QUALITY
GUARANTEED

on
the
Go
PACKS
Cold

Cold
Acetaminophen, Dextromethorphan HBr, Guaifenesin, Phenylephrine HCl
Pain Reliever/Fever Reducer, Cough Suppressant, Expectorant, Nasal Decongestant

Non-Drowsy Relief of

- Cough, Impulse to Cough
- Nasal Congestion
- Sore Throat

SEVERE
CONGESTION

6
Tablets
3 POUCHES, 2 TABLETS PER POUCH

Lil'
DrugStore®

PRINCIPAL DISPLAY PANEL - 20 Tablet Carton - 9828

EZ Paks™
Stores & Travels Easily!

Compare to the active ingredients in
Tylenol® Cold Head Congestion*

NON-DROWSY FORMULA

Cold Relief
Pain Reliever/Fever Reducer, Expectorant, Nasal Decongestant, Cough Suppressant

SEVERE CONGESTION

Contains 4 Active Medicines:
Acetaminophen... relieves Headache, Sore Throat

Dextromethorphan HBr...relieves Coughing

Guaifenesin...relieves Chest Congestion

Phenylephrine HCl...relieves Nasal Congestion

20 TABLETS
IN 10 POUCHES OF 2 TABLETS

Lil'
Drug Store®